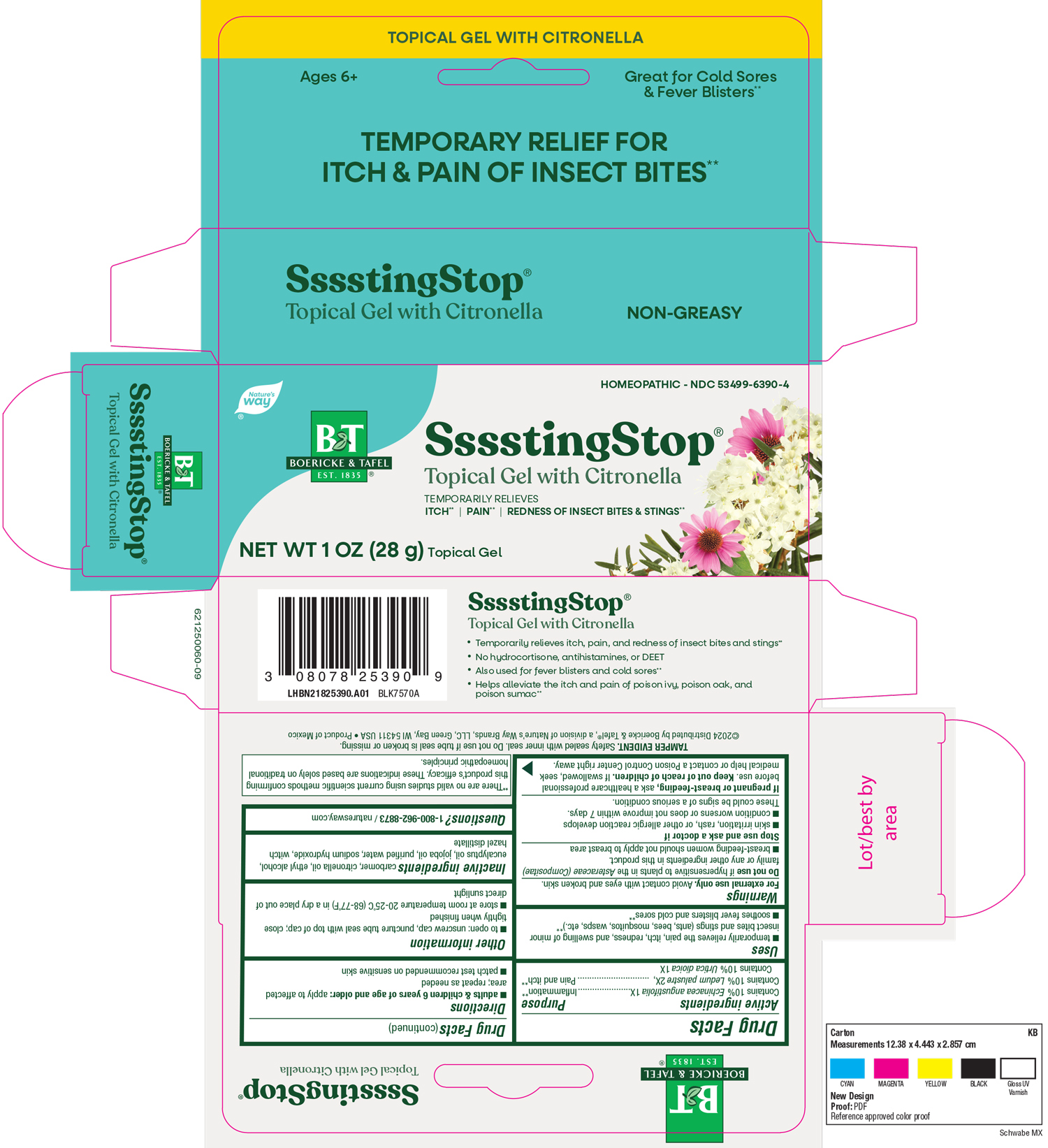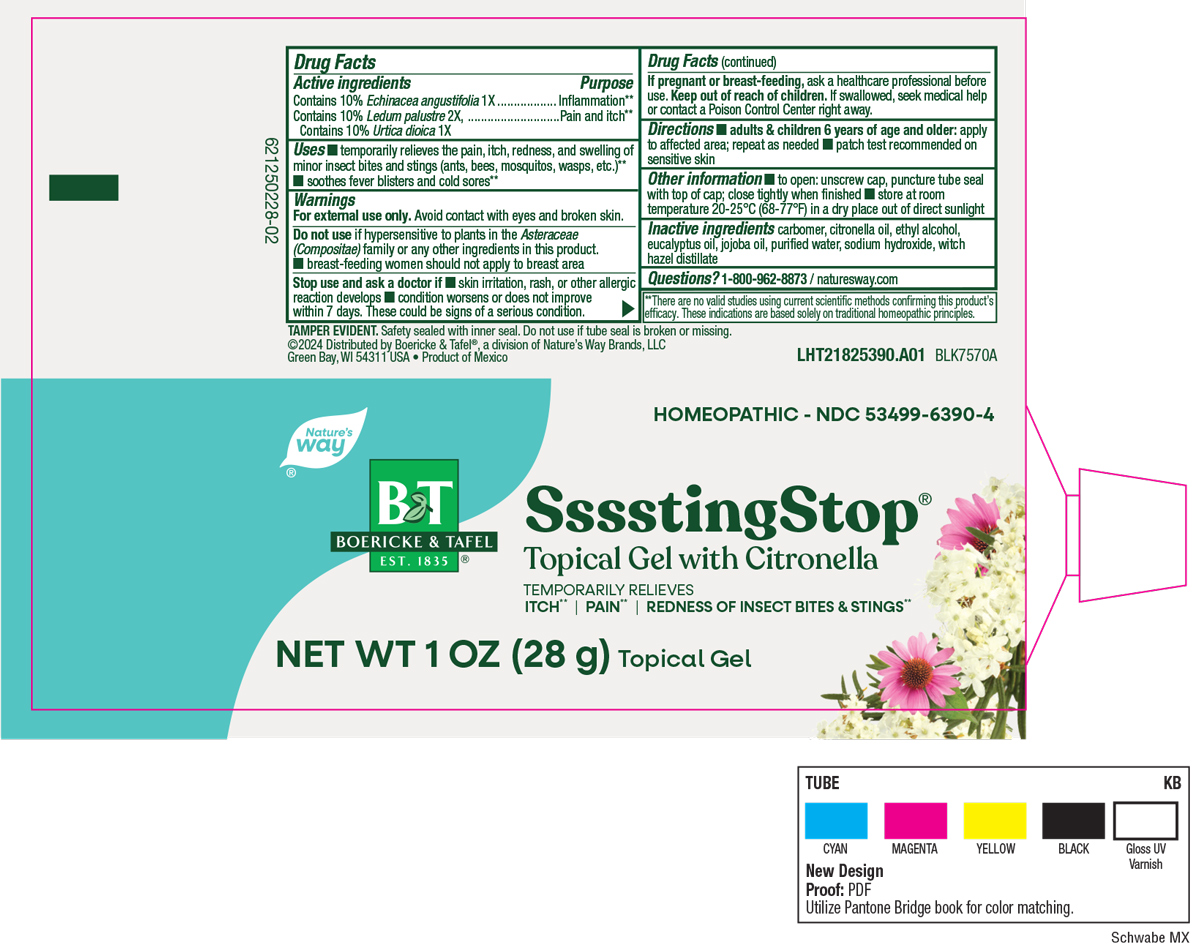 DRUG LABEL: Ssssting Stop Gel
NDC: 68466-2006 | Form: GEL
Manufacturer: Schwabe Mexico, S.A. de C.V.
Category: homeopathic | Type: HUMAN OTC DRUG LABEL
Date: 20251118

ACTIVE INGREDIENTS: Echinacea Angustifolia 1 [hp_X]/78 g; Ledum Palustre Twig 2 [hp_X]/78 g; Urtica Dioica 1 [hp_X]/78 g
INACTIVE INGREDIENTS: CITRONELLA OIL; ALCOHOL; EUCALYPTUS OIL; JOJOBA OIL; CARBOMER HOMOPOLYMER TYPE C; WATER; SODIUM HYDROXIDE; WITCH HAZEL

SSSSTING STOP GEL

Active Ingredients

Echinacia angustifolia 1X

Ledum palustre 2X

Urtica dioica 1X

Inactive Ingredients

Carbomer

Citronella Oil

Ethyl Alcohol

Eucalyptus Oil

Jojoba Oil

Purified Water

Sodium Hydroxide

Witch Hazel Distillate

Dosage & Administration

Directions:

Adults and children 6 years of age and older: apply to affected area; repeat as needed.

Patch test recommended on sensitive skin.

Purpose

Temporarily relieves the pain, itch, redness, and swelling of minor insect bites and stings (ants, bees, mosquitos, wasps, etc).

Soothes fever blisters and cold sores.

Indications & Usage

Temporarily relieves the pain, itch, redness, and swelling of minor insect bites and stings (ants, bees, mosquitos, wasps, etc).

Soothes fever blisters and cold sores.

Warnings

For external use only. Avoid contact with eyes and broken skin.

Do not use if hypersensitive to plants in the Asteraceae (Compositae) family or any other ingredients in this product.

Breast-feeding women should not apply to breast area.

Stop Use

Stop use and ask a doctor if skin irritation, rash, or other allergic reaction develops, condition worsens or does not improve within 7 days.

These could be signs of a serious condition.

Pregnancy or Breast feeding

If pregnant or breast-feeding, consult a healthcare professional before use.

Keep out of reach of children

Overdose

If swallowed, seek medical help or contact a Poison Control Center right away.